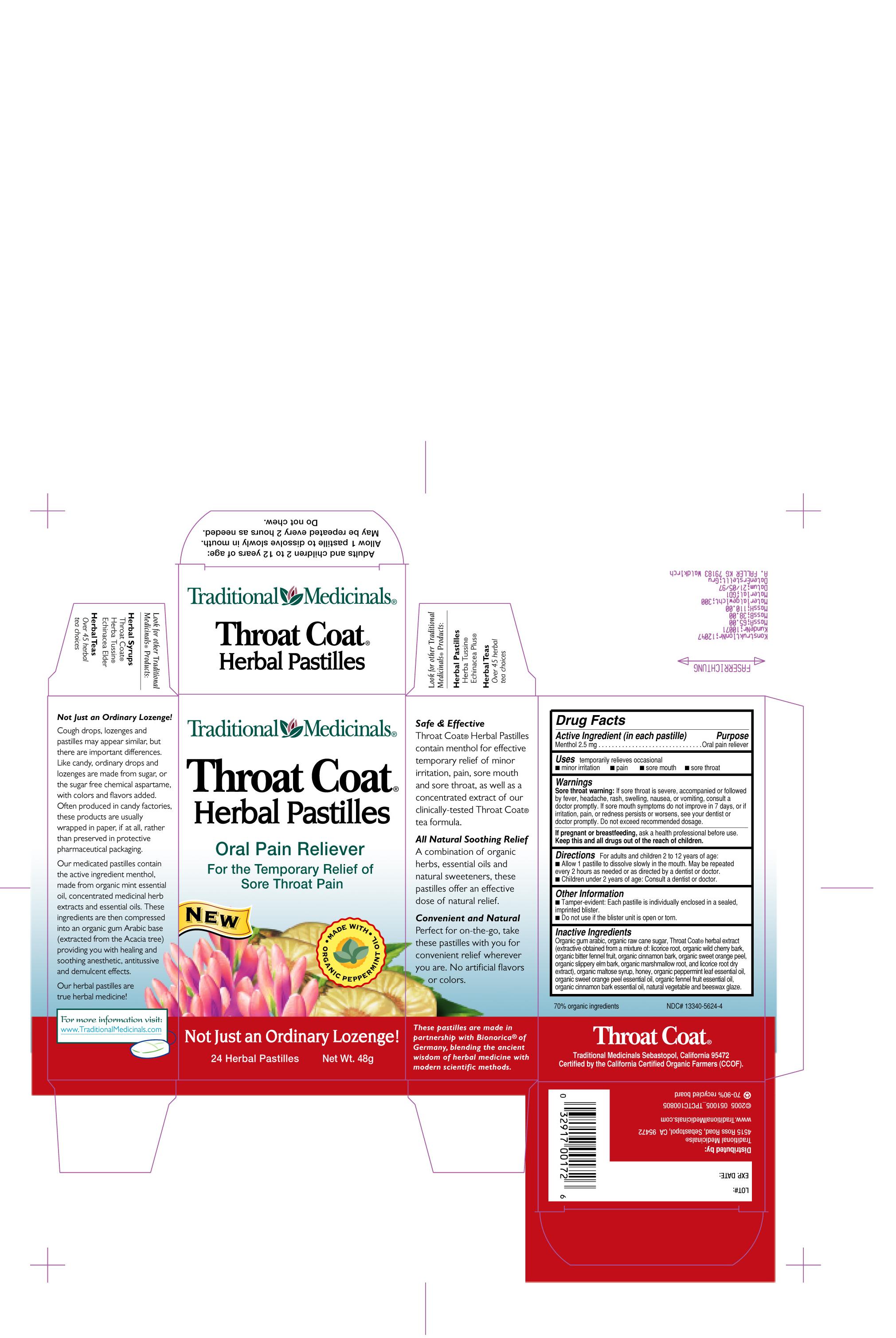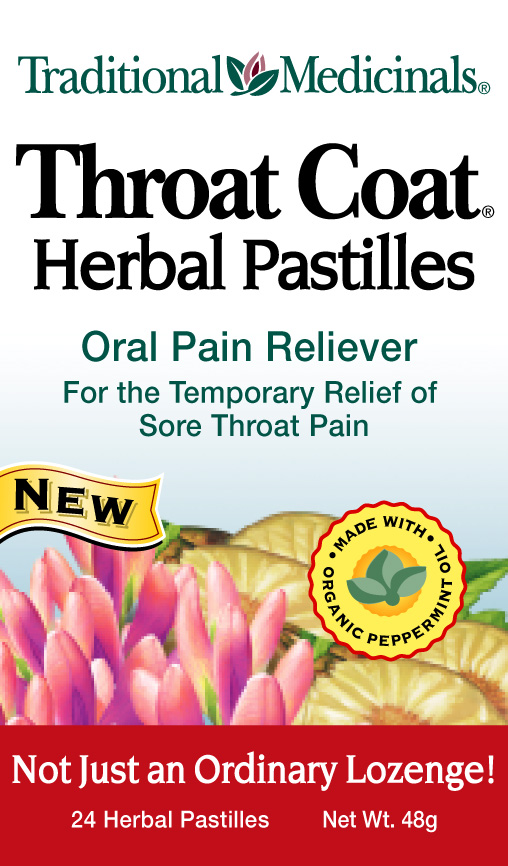 DRUG LABEL: Throat Coat 
NDC: 13340-5624 | Form: PASTILLE
Manufacturer: Phytoneering Extract Solutions GmbH
Category: otc | Type: HUMAN OTC DRUG LABEL
Date: 20100630

ACTIVE INGREDIENTS: Menthol 2.5 mg/1 1
INACTIVE INGREDIENTS: Acacia; Raw Sugar; Maltose Syrup; Honey; Fennel Oil; Cinnamon Bark Oil; Orange Oil; Peppermint Oil

Warnings
Sore throat warning: If sore throat is severe, accompanied or followed
by fever, headache, rash, swelling, nausea, or vomiting, consult a
doctor promptly. If sore mouth symptoms do not improve in 7 days, or if
irritation, pain, or redness persists or worsens, see your dentist or
doctor promptly. Do not exceed recommended dosage.
If pregnant or breastfeeding, ask a health professional before use.
Keep this and all drugs out of the reach of children.

Active Ingredient (in each pastille) Purpose
Menthol 2.5 mg . . . . . . . . . . . . . . . . . . . . . . . . . . . . . . . Oral pain reliever

PURPOSE

Uses: temporarily relieves occasional minor irritation, pain, sore mouth, sore throat

DOSAGE AND ADMINISTRATION

Directions For adults and children 2 to 12 years of age: Allow 1 pastille to dissolve slowly in the mouth. May be repeated
every 2 hours as needed or as directed by a dentist or doctor. Children under 2 years of age: Consult a dentist or doctor.

Inactive Ingredients
Organic gum arabic, organic raw cane sugar, Throat Coat® herbal extract
(extractive obtained from a mixture of: licorice root, organic wild cherry bark,
organic bitter fennel fruit, organic cinnamon bark, organic sweet orange peel,
organic slippery elm bark, organic marshmallow root, and licorice root dry
extract), organic maltose syrup, honey, organic peppermint leaf essential oil,
organic sweet orange peel essential oil, organic fennel fruit essential oil,
organic cinnamon bark essential oil, natural vegetable and beeswax glaze.

Other Information
Tamper-evident: Each pastille is individually enclosed in a sealed, imprinted blister. Do not use if the blister unit is open or torn.

PACKAGE LABEL

Enter section text here

Principal Display Panel image
Carton image